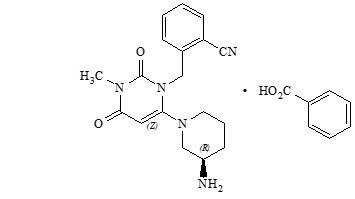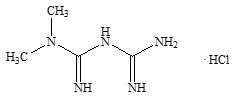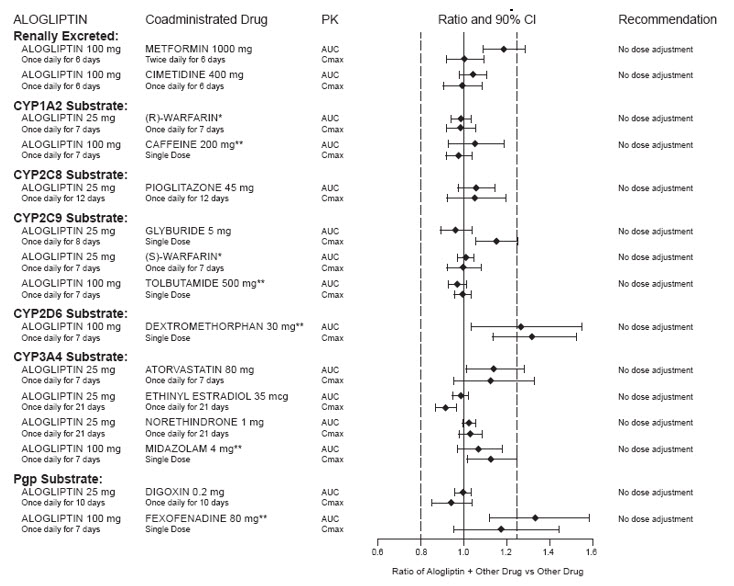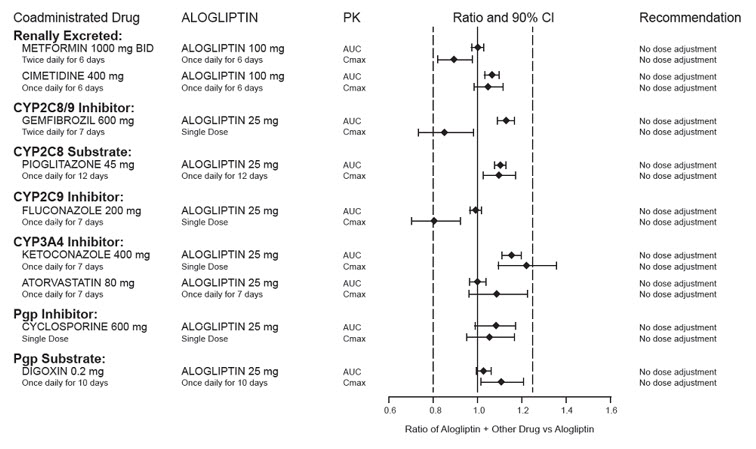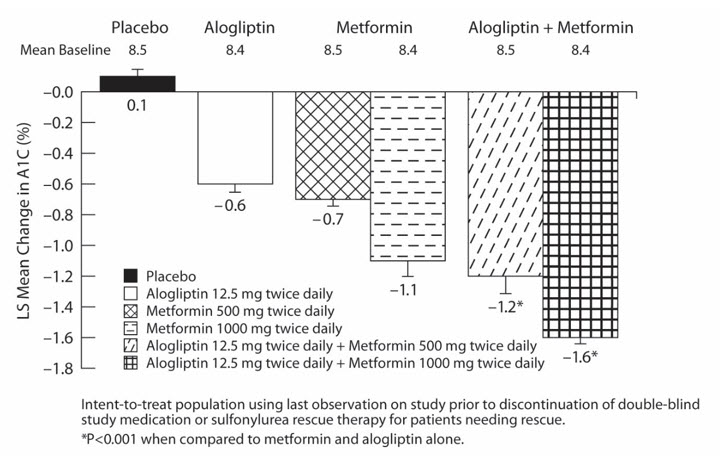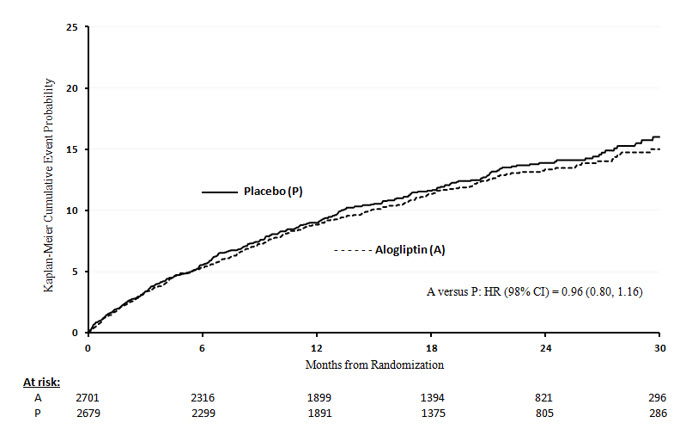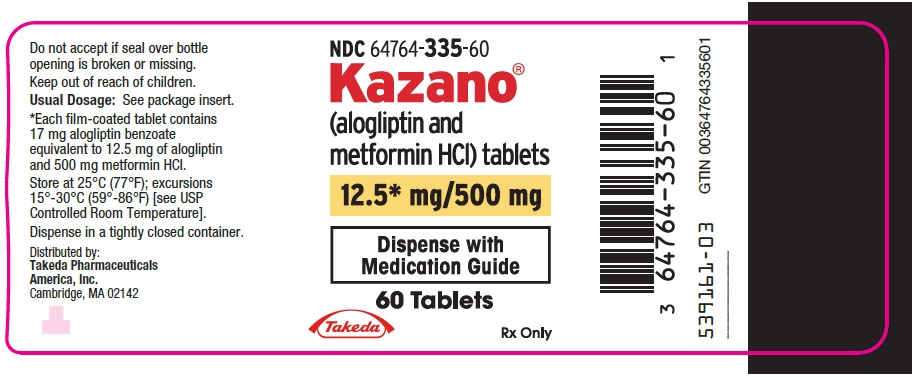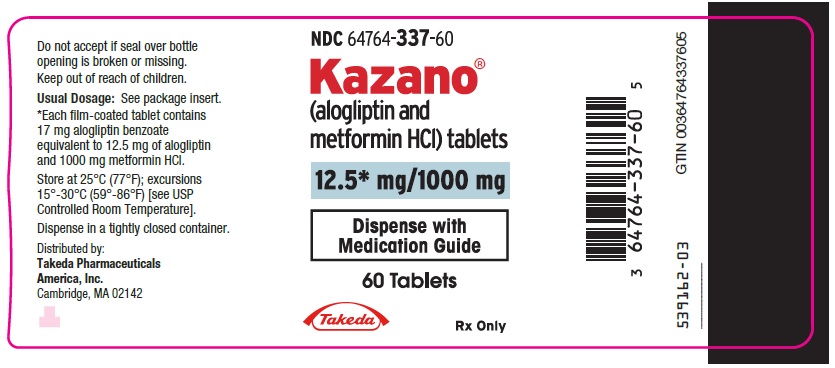 DRUG LABEL: KAZANO
NDC: 64764-335 | Form: TABLET, FILM COATED
Manufacturer: Takeda Pharmaceuticals America, Inc.
Category: prescription | Type: HUMAN PRESCRIPTION DRUG LABEL
Date: 20250530

ACTIVE INGREDIENTS: ALOGLIPTIN BENZOATE 12.5 mg/1 1; Metformin hydrochloride 500 mg/1 1
INACTIVE INGREDIENTS: mannitol; microcrystalline cellulose; POVIDONE, UNSPECIFIED; CROSPOVIDONE, UNSPECIFIED; magnesium stearate; talc; titanium dioxide; ferric oxide yellow; HYPROMELLOSE 2910 (6 MPA.S)

HIGHLIGHTS OF PRESCRIBING INFORMATION

These highlights do not include all the information needed to use KAZANO® safely and effectively. See full prescribing information for KAZANO.
KAZANO (alogliptin and metformin hydrochloride) tablets, for oral use
Initial U.S. Approval: 2013

WARNING: LACTIC ACIDOSIS

See full prescribing information for complete boxed warning.

- Postmarketing cases of metformin-associated lactic acidosis have resulted in death, hypothermia, hypotension, and resistant bradyarrhythmias. Symptoms included malaise, myalgias, respiratory distress, somnolence, and abdominal pain. Laboratory abnormalities included elevated blood lactate levels, anion gap acidosis, increased lactate/pyruvate ratio; and metformin plasma levels generally greater than 5 mcg/mL. (5.1)
- Risk factors include renal impairment, concomitant use of certain drugs, age ≥65 years old, radiological studies with contrast, surgery and other procedures, hypoxic states, excessive alcohol intake, and hepatic impairment. Steps to reduce the risk of and manage metformin-associated lactic acidosis in these high risk groups are provided in the Full Prescribing Information. (5.1)
- If lactic acidosis is suspected, discontinue KAZANO and institute general supportive measures in a hospital setting. Prompt hemodialysis is recommended. (5.1)

1 INDICATIONS AND USAGE

KAZANO is a combination of alogliptin, a dipeptidyl-peptidase-4 (DPP-4) inhibitor and metformin hydrochloride (HCl), a biguanide, indicated as an adjunct to diet and exercise to improve glycemic control in adults with type 2 diabetes mellitus. (1)

Limitations of Use: Should not be used in patients with type 1 diabetes mellitus. (1)

2 DOSAGE AND ADMINISTRATION

- Individualize the starting dosage based on the patient's current regimen. (2.1)
- Given orally twice daily with food. (2.1)
- Adjust the dosage based on effectiveness and tolerability while not exceeding the maximum recommended daily dosage of 25 mg alogliptin and 2000 mg metformin HCl. (2.1)
- Prior to initiation, assess renal function with estimated glomerular filtration rate (eGFR). (2.2)
  - Do not use in patients with eGFR below 60 mL/min/1.73 m^2.
- KAZANO may need to be discontinued at time of, or prior to, iodinated contrast imaging procedures. (2.3)

3 DOSAGE FORMS AND STRENGTHS

Tablets:12.5 mg alogliptin and 500 mg metformin HCl, 12.5 mg alogliptin and 1000 mg metformin HCl. (3)

4 CONTRAINDICATIONS

- Severe renal impairment: eGFR below 30 mL/min/1.73 m^2. (4)
- Metabolic acidosis, including diabetic ketoacidosis. (4)
- History of serious hypersensitivity to alogliptin or metformin, components of KAZANO or any of the excipients. (4)

5 WARNINGS AND PRECAUTIONS

- Lactic acidosis: See boxed warning. (5.1)
- Pancreatitis: There have been postmarketing reports of acute pancreatitis. If pancreatitis is suspected, promptly discontinue KAZANO. (5.2)
- Heart failure: Consider the risks and benefits of KAZANO prior to initiating treatment in patients at risk for heart failure. If heart failure develops, evaluate and manage according to current standards of care and consider discontinuation of KAZANO. (5.3)
- Hypersensitivity: There have been postmarketing reports of serious hypersensitivity reactions in patients treated with alogliptin such as anaphylaxis, angioedema and severe cutaneous adverse reactions, including Stevens-Johnson syndrome. If hypersensitivity reactions occur, discontinue KAZANO, treat promptly, and monitor until signs and symptoms resolve. (5.4)
- Hepatic effects: Postmarketing reports of hepatic failure, sometimes fatal. Causality cannot be excluded. If liver injury is detected, promptly interrupt KAZANO and assess patient for probable cause, then treat cause if possible, to resolution or stabilization. Do not restart KAZANO if liver injury is confirmed and no alternative etiology can be found. (5.5)
- Vitamin B12 deficiency: Metformin may lower vitamin B12 levels. Measure hematologic parameters annually and B12 at 2 to 3 year intervals and manage any abnormalties. (5.6)
- Hypoglycemia: Consider lowering the dosage of insulin secretagogue or insulin to reduce the risk of hypoglycemia when initiating KAZANO. (5.7)
- Arthralgia: Severe and disabling arthralgia has been reported in patients taking DPP-4 inhibitors. Consider as a possible cause for severe joint pain and discontinue drug if appropriate. (5.8)
- Bullous pemphigoid: There have been postmarketing reports of bullous pemphigoid requiring hospitalization in patients taking DPP-4 inhibitors. Tell patients to report development of blisters or erosions. If bullous pemphigoid is suspected, discontinue KAZANO. (5.9)

6 ADVERSE REACTIONS

Most common adverse reactions (incidence ≥4%) are upper respiratory tract infection, nasopharyngitis, diarrhea, hypertension, headache, back pain and urinary tract infection. (6.1)

To report SUSPECTED ADVERSE REACTIONS, contact Takeda Pharmaceuticals America, Inc. at 1-877-TAKEDA-7 (1-877-825-3327) or FDA at 1-800-FDA-1088 or www.fda.gov/medwatch.

7 DRUG INTERACTIONS

- Carbionic anhydrase inhibitors may increase risk of lactic acidosis. Consider more frequent monitoring. (7)
- Drugs that reduce metformin clearance (such as ranolazine, vandetanib, dolutegravir, and cimetidine), may increase the accumulation of metformin. Consider the benefits and risks of concomitant use. (7)
- Alcohol can potentiate the effect of metformin on lactate metabolism. Warn patients against excessive alcohol intake. (7)

8 USE IN SPECIFIC POPULATIONS

- Females and Males of Reproductive Potential: Advise premenopausal females of the potential for an unintended pregnancy. (8.3)
- Pediatrics: Safety and effectiveness of KAZANO in pediatric patients have not been established. (8.4)
- Geriatric Use: Assess renal function more frequently. (8.5)
- Hepatic Impairment: Avoid use in patients with hepatic impairment. (8.7)

FULL PRESCRIBING INFORMATION

WARNING: LACTIC ACIDOSIS

Postmarketing cases of metformin-associated lactic acidosis have resulted in death, hypothermia, hypotension, and resistant bradyarrhythmias. The onset of metformin-associated lactic acidosis is often subtle, accompanied only by nonspecific symptoms such as malaise, myalgias, respiratory distress, somnolence, and abdominal pain. Metformin-associated lactic acidosis was characterized by elevated blood lactate levels (greater than 5 mmol/L), anion gap acidosis (without evidence of ketonuria or ketonemia), an increased lactate/pyruvate ratio; and metformin plasma levels generally greater than 5 mcg/mL [see Warnings and Precautions (5.1)].

Risk factors for metformin-associated lactic acidosis include renal impairment, concomitant use of certain drugs (e.g., carbonic anhydrase inhibitors such as topiramate), age 65 years old or greater, having a radiological study with contrast, surgery and other procedures, hypoxic states (e.g., acute congestive heart failure), excessive alcohol intake, and hepatic impairment.

Steps to reduce the risk of and manage metformin-associated lactic acidosis in these high risk groups are provided in the Full Prescribing Information [see Dosage and Administration (2.2), Contraindications (4), Warnings and Precautions (5.1), Drug Interactions (7), Use in Specific Populations (8.6, 8.7)].

If metformin-associated lactic acidosis is suspected, immediately discontinue KAZANO® and institute general supportive measures in a hospital setting. Prompt hemodialysis is recommended [see Warnings and Precautions (5.1)].

1 INDICATIONS AND USAGE

KAZANO is indicated as an adjunct to diet and exercise to improve glycemic control in adults with type 2 diabetes mellitus.

Limitations of Use

KAZANO is not recommended for use in patients with type 1 diabetes mellitus.

2 DOSAGE AND ADMINISTRATION

2.1 Recommended Dosage

- Individualize the starting dosage of KAZANO based on the patient's current regimen.
- KAZANO should be taken orally twice daily with food with gradual dose escalation to reduce the gastrointestinal (GI) side effects due to metformin. Do not split tablets.
- Adjust the dosage based on effectiveness and tolerability while not exceeding the maximum recommended daily dose of 25 mg alogliptin and 2000 mg metformin hydrochloride (HCl).

2.2 Recommendations for Use in Renal Impairment

Assess renal function prior to initiation of KAZANO and periodically thereafter.

KAZANO is contraindicated in patients with an estimated glomerular filtration rate (eGFR) below 30 mL/min/1.73 m^2 [see Contraindications (4), Warnings and Precautions (5.1)].

KAZANO is not recommended in patients with an eGFR between 30 and 59 mL/min/1.73 m^2 because these patients require a lower daily dosage of alogliptin than what is available in the fixed combination KAZANO product.

Kazano requires no dose adjustment in patients with an eGFR of 60 mL/min/1.73 m^2 or greater.

2.3 Discontinuation for Iodinated Contrast Imaging Procedures

Discontinue KAZANO at the time of, or prior to, an iodinated contrast imaging procedure in patients with an eGFR between 30 and 60 mL/min/1.73 m^2; in patients with a history of liver disease, alcoholism or heart failure; or in patients who will be administered intra-arterial iodinated contrast. Re-evaluate eGFR 48 hours after the imaging procedure; restart KAZANO if renal function is stable [see Warnings and Precautions (5.1)].

3 DOSAGE FORMS AND STRENGTHS

- 12.5 mg/500 mg tablets are pale yellow, oblong, film-coated tablets with "12.5/500" debossed on one side and "322M" debossed on the other side
- 12.5 mg/1000 mg tablets are pale yellow, oblong, film-coated tablets with "12.5/1000" debossed on one side and "322M" debossed on the other side

4 CONTRAINDICATIONS

KAZANO is contraindicated in patients with:

- Severe renal impairment (eGFR below 30 mL/min/1.73 m^2) [see Warnings and Precautions (5.1)].
- Acute or chronic metabolic acidosis, including diabetic ketoacidosis with or without coma.
- History of serious hypersensitivity reaction to alogliptin or metformin or any of the excipients in KAZANO, such as anaphylaxis, angioedema and severe cutaneous adverse reactions [see Warnings and Precautions (5.4), Adverse Reactions (6.2)].

5 WARNINGS AND PRECAUTIONS

5.1 Lactic Acidosis

Lactic Acidosis

There have been postmarketing cases of metformin-associated lactic acidosis, including fatal cases. These cases had a subtle onset and were accompanied by nonspecific symptoms such as malaise, myalgias, abdominal pain, respiratory distress, or increased somnolence; however, hypothermia, hypotension and resistant bradyarrhythmias have occurred with severe acidosis. Metformin-associated lactic acidosis was characterized by elevated blood lactate concentrations (greater than 5 mmol/L), anion gap acidosis (without evidence of ketonuria or ketonemia), and an increased lactate:pyruvate ratio; metformin plasma levels generally greater than 5 mcg/mL. Metformin decreases liver uptake of lactate increasing lactate blood levels which may increase the risk of lactic acidosis, especially in patients at risk.

If metformin-associated lactic acidosis is suspected, general supportive measures should be instituted promptly in a hospital setting, along with immediate discontinuation of KAZANO. In KAZANO-treated patients with a diagnosis or strong suspicion of lactic acidosis, prompt hemodialysis is recommended to correct the acidosis and remove accumulated metformin (metformin HCl is dialyzable, with a clearance of up to 170 mL/min under good hemodynamic conditions). Hemodialysis has often resulted in reversal of symptoms and recovery.

Educate patients and their families about the symptoms of lactic acidosis and if these symptoms occur instruct them to discontinue KAZANO and report these symptoms to their healthcare provider.

For each of the known and possible risk factors for metformin-associated lactic acidosis, recommendations to reduce the risk of and manage metformin-associated lactic acidosis are provided below:

Renal Impairment

The postmarketing metformin-associated lactic acidosis cases primarily occurred in patients with significant renal impairment. The risk of metformin accumulation and metformin-associated lactic acidosis increases with the severity of renal impairment because metformin is substantially excreted by the kidney. Clinical recommendations based upon the patient's renal function include [see Dosage and Administration (2.2), Clinical Pharmacology (12.3)]:

- Before initiating KAZANO, obtain an eGFR.
- KAZANO is contraindicated in patients with an eGFR less than 30 mL/min/1.73 m^2 [see Contraindications (4)].
- KAZANO is not recommended in patients with an eGFR between 30 and 60 mL/min/1.73 m^2 because these patients require a lower dosage of alogliptin than what is available in the fixed combination KAZANO product.
- Obtain an eGFR at least annually in all patients taking KAZANO. In patients at increased risk for the development of renal impairment (e.g., the elderly), renal function should be assessed more frequently.

Drug Interactions

The concomitant use of KAZANO with specific drugs may increase the risk of metformin-associated lactic acidosis: those that impair renal function, result in significant hemodynamic change, interfere with acid-base balance or increase metformin accumulation [see Drug Interactions (7)]. Therefore, consider more frequent monitoring of patients.

Age 65 or Greater

The risk of metformin-associated lactic acidosis increases with the patient's age because elderly patients have a greater likelihood of having hepatic, renal, or cardiac impairment than younger patients. Assess renal function more frequently in elderly patients [see Use in Specific Populations (8.5)].

Radiological Studies with Contrast

Administration of intravascular iodinated contrast agents in metformin-treated patients has led to an acute decrease in renal function and the occurrence of lactic acidosis. Stop KAZANO at the time of, or prior to, an iodinated contrast imaging procedure in patients with an eGFR between 30 and 60 mL/min/1.73 m^2; in patients with a history of hepatic impairment, alcoholism, or heart failure; or in patients who will be administered intra-arterial iodinated contrast. Re-evaluate eGFR 48 hours after the imaging procedure, and restart KAZANO if renal function is stable.

Surgery and Other Procedures

Withholding of food and fluids during surgical or other procedures may increase the risk for volume depletion, hypotension and renal impairment. KAZANO should be temporarily discontinued while patients have restricted food and fluid intake.

Hypoxic States

Several of the postmarketing cases of metformin-associated lactic acidosis occurred in the setting of acute congestive heart failure (particularly when accompanied by hypoperfusion and hypoxemia). Cardiovascular collapse (shock), acute myocardial infarction, sepsis, and other conditions associated with hypoxemia have been associated with lactic acidosis and may also cause prerenal azotemia. When such events occur, discontinue KAZANO.

Excessive Alcohol Intake

Alcohol potentiates the effect of metformin on lactate metabolism and this may increase the risk of metformin-associated lactic acidosis. Warn patients against excessive alcohol intake while receiving KAZANO.

Hepatic Impairment

Patients with hepatic impairment have developed with cases of metformin-associated lactic acidosis. This may be due to impaired lactate clearance resulting in higher lactate blood levels. Therefore, avoid use of KAZANO in patients with clinical or laboratory evidence of hepatic disease.

5.2 Pancreatitis

Acute pancreatitis has been reported in the postmarketing setting and in randomized clinical trials. In glycemic control trials in patients with type 2 diabetes mellitus, acute pancreatitis was reported in 6 (0.2%) patients treated with alogliptin 25 mg and 2 (<0.1%) patients treated with active comparators or placebo. In the EXAMINE trial (a cardiovascular outcomes trial of patients with type 2 diabetes mellitus and high cardiovascular (CV) risk), acute pancreatitis was reported in 10 (0.4%) patients treated with alogliptin and in 7 (0.3%) patients treated with placebo.

It is unknown whether patients with a history of pancreatitis are at increased risk for pancreatitis while using KAZANO.

After initiation of KAZANO, patients should be observed for signs and symptoms of pancreatitis. If pancreatitis is suspected, alogliptin should promptly be discontinued and appropriate management should be initiated.

5.3 Heart Failure

In the EXAMINE trial which enrolled patients with type 2 diabetes mellitus and recent acute coronary syndrome, 106 (3.9%) of patients treated with alogliptin and 89 (3.3%) of patients treated with placebo were hospitalized for congestive heart failure.

Consider the risks and benefits of KAZANO prior to initiating treatment in patients at risk for heart failure, such as those with a prior history of heart failure and a history of renal impairment, and observe these patients for signs and symptoms of heart failure during therapy. Patients should be advised of the characteristic symptoms of heart failure and should be instructed to immediately report such symptoms. If heart failure develops, evaluate and manage according to current standards of care and consider discontinuation of KAZANO.

5.4 Hypersensitivity Reactions

There have been postmarketing reports of serious hypersensitivity reactions in patients treated with alogliptin [see Adverse Reactions (6.2)]. These reactions include anaphylaxis, angioedema and severe cutaneous adverse reactions, including Stevens-Johnson syndrome. If a serious hypersensitivity reaction is suspected, discontinue KAZANO, assess for other potential causes for the event and institute alternative treatment for diabetes mellitus. Use caution in patients with a history of angioedema with another dipeptidyl peptidase-4 (DPP-4) inhibitor because it is unknown whether such patients will be predisposed to angioedema with KAZANO.

5.5 Hepatic Effects

There have been postmarketing reports of fatal and nonfatal hepatic failure in patients taking alogliptin, although some of the reports contain insufficient information necessary to establish the probable cause [see Adverse Reactions (6.2)].

In glycemic control trials in patients with type 2 diabetes mellitus, serum alanine aminotransferase (ALT) elevations greater than three times the upper limit of normal (ULN) were reported in 1.3% of patients treated with alogliptin 25 mg and 1.7% of patients treated with active comparators or placebo. In the EXAMINE trial (a cardiovascular outcomes trial of patients with type 2 diabetes mellitus and high cardiovascular (CV) risk), increases in serum alanine aminotransferase three times the upper limit of the reference range occurred in 2.4% of patients treated with alogliptin and in 1.8% of patients treated with placebo.

Measure liver tests promptly in patients who report symptoms that may indicate liver injury, including fatigue, anorexia, right upper abdominal discomfort, dark urine or jaundice. In this clinical context, if the patient is found to have clinically significant liver enzyme elevations and if abnormal liver tests persist or worsen, KAZANO should be interrupted and investigation done to establish the probable cause. KAZANO should not be restarted in these patients without another explanation for the liver test abnormalities.

5.6 Vitamin B12 Levels

In metformin clinical trials of 29 week duration, a decrease to subnormal levels of previously normal serum vitamin B12 levels was observed in approximately 7% of patients. Such decrease, possibly due to interference with B12 absorption from the B12-intrinsic factor complex, may be associated with anemia but appears to be rapidly reversible with discontinuation of metformin or vitamin B12 supplementation. Certain individuals (those with inadequate vitamin B12 or calcium intake or absorption) appear to be predisposed to developing subnormal vitamin B12 levels. Measure hematologic parameters on an annual basis and vitamin B12 at 2 to 3 year intervals in patients on KAZANO and manage any abnormalities [see Adverse Reactions (6.1)].

5.7 Hypoglycemia with Concomitant Use with Insulin or Insulin Secretagogues

Insulin and insulin secretagogues, such as sulfonylureas, are known to cause hypoglycemia. Therefore, a lower dosage of insulin or insulin secretagogue may be required to minimize the risk of hypoglycemia when used in combination with KAZANO.

5.8 Severe and Disabling Arthralgia

There have been postmarketing reports of severe and disabling arthralgia in patients taking DPP-4 inhibitors. The time to onset of symptoms following initiation of drug therapy varied from one day to years. Patients experienced relief of symptoms upon discontinuation of the medication. A subset of patients experienced a recurrence of symptoms when restarting the same drug or a different DPP-4 inhibitor. Consider DPP-4 inhibitors as a possible cause for severe joint pain and discontinue drug if appropriate.

5.9 Bullous Pemphigoid

Postmarketing cases of bullous pemphigoid requiring hospitalization have been reported with DPP-4 inhibitor use. In reported cases, patients typically recovered with topical or systemic immunosuppressive treatment and discontinuation of DPP-4 inhibitor. Tell patients to report development of blisters or erosions while receiving KAZANO. If bullous pemphigoid is suspected, KAZANO should be discontinued and referral to a dermatologist should be considered for diagnosis and appropriate treatment.

6 ADVERSE REACTIONS

The following serious adverse reactions are described below or elsewhere in the prescribing information:

- Pancreatitis [see Warnings and Precautions (5.2)]
- Heart Failure [see Warnings and Precautions (5.3)]
- Hypersensitivity Reactions [see Warnings and Precautions (5.4)]
- Hepatic Effects [see Warnings and Precautions (5.5)]
- Severe and Disabling Arthralgia [see Warnings and Precautions (5.8)]
- Bullous Pemphigoid [see Warnings and Precautions (5.9)]

6.1 Clinical Trials Experience

Because clinical trials are conducted under widely varying conditions, adverse reaction rates observed in the clinical trials of a drug cannot be directly compared to rates in the clinical trials of another drug and may not reflect the rates observed in practice.

Alogliptin and Metformin HCl

Over 2,700 patients with type 2 diabetes mellitus have received alogliptin coadministered with metformin in four large, randomized, double-blind controlled clinical trials. The racial distribution of patients exposed to trial medication was 65% White, 20% Asian, 7% Black or African American, 4% American Indian or Alaska Native, 0% Native Hawaiian/Other Pacific Islander and 4% Multiracial or other racial groups. The ethnic distribution was 23% Hispanic or Latino and 77% was not Hispanic or Latino. The mean exposure to alogliptin coadministered with metformin was 58 weeks, with more than 1,400 subjects treated for more than one year. These included two 26 week placebo-controlled trials, one 52 week active control trial and an interim analysis of a 104 week active-controlled trial. In the alogliptin co-administered with metformin HCl arm, the mean duration of diabetes mellitus was approximately six years, the mean body mass index (BMI) was 31 kg/m^2 (56% of patients had a BMI ≥30 kg/m^2) and the mean age was 55 years (18% of patients ≥65 years of age).

In a pooled analysis of these four controlled clinical studies, the overall incidence of adverse reactions was 74% in patients treated with alogliptin co-administered with metformin HCl compared to 75% treated with placebo. Overall discontinuation of therapy due to adverse reactions was 6.2% with alogliptin co-administered with metformin HCl compared to 1.9% in placebo, 6.4% in metformin and 5.0% in alogliptin.

Adverse reactions reported in ≥4% of patients treated with alogliptin co-administered with metformin HCl and more frequently than in patients who received alogliptin, metformin or placebo are summarized in Table 1.

Table 1. Adverse Reactions Reported in ≥4% of Adults with Type 2 Diabetes Mellitus Treated with Alogliptin Co-administered with Metformin HCl and More Frequently Than in Patients Receiving Either Alogliptin, Metformin or Placebo
 | Number of Patients (%)
 | Alogliptin and Metformin [Alogliptin and metformin – includes data pooled for patients receiving alogliptin 25 and 12.5 mg combined with various doses of metformin] | Alogliptin [Alogliptin – includes data pooled for patients receiving alogliptin 25 and 12.5 mg] | Metformin [Metformin – includes data pooled for patients receiving various doses of metformin] | Placebo
 | N=2794 | N=222 | N=1592 | N=106
Upper respiratory tract infection | 224 (8) | 6 (3) | 105 (7) | 3 (3)
Nasopharyngitis | 191 (7) | 7 (3) | 93 (6) | 2 (2)
Diarrhea | 155 (6) | 4 (2) | 105 (7) | 3 (3)
Hypertension | 154 (6) | 5 (2) | 96 (6) | 6 (6)
Headache | 149 (5) | 11 (5) | 74 (5) | 3 (3)
Back pain | 119 (4) | 1 (1) | 72 (5) | 1 (1)
Urinary tract infection | 116 (4) | 4 (2) | 59 (4) | 2 (2)

Alogliptin

A total of 14,778 patients with type 2 diabetes mellitus participated in 14 randomized, double-blind, controlled clinical trials of whom 9,052 subjects were treated with alogliptin, 3,469 subjects were treated with placebo and 2,257 were treated with an active comparator. The racial distribution of patients exposed to trial medication was 71% White, 17% Asian, 6% Black or African American, 2% American Indian or Alaska Native, 0% Native Hawaiian/Other Pacific Islander and 5% Multiracial or other racial groups. The ethnic distribution was 30% Hispanic or Latino and 70% was not Hispanic or Latino. The mean duration of diabetes mellitus was seven years, the mean body mass index (BMI) was 31 kg/m^2 (49% of patients had a BMI ≥30 kg/m^2), and the mean age was 58 years (26% of patients ≥65 years of age). The mean exposure to alogliptin was 49 weeks with 3,348 subjects treated for more than one year.

In a pooled analysis of these 14 controlled clinical trials, the overall incidence of adverse reactions was 73% in patients treated with alogliptin 25 mg compared to 75% with placebo and 70% with active comparator. Overall discontinuation of therapy due to adverse reactions was 6.8% with alogliptin 25 mg compared to 8.4% with placebo or 6.2% with active comparator.

Adverse reactions reported in ≥4% of patients treated with alogliptin 25 mg and more frequently than in patients who received placebo are summarized in Table 2.

Table 2. Adverse Reactions Reported in ≥4% Patients Treated with Alogliptin 25 mg and More Frequently Than in Patients Given Placebo in Pooled Studies
 | Number of Patients (%)
 | Alogliptin 25 mg | Placebo | Active Comparator
 | N=6447 | N=3469 | N=2257
Nasopharyngitis | 309 (5) | 152 (4) | 113 (5)
Upper Respiratory Tract Infection | 287 (5) | 121 (4) | 113 (5)
Headache | 278 (4) | 101 (3) | 121 (5)

Hypoglycemia

Alogliptin and Metformin HCl

In a 26 week, double-blind, placebo-controlled trial of alogliptin in combination with metformin, the number of patients reporting hypoglycemia was 1.9% in the alogliptin 12.5 mg with metformin HCl 500 mg, 5.3% in the alogliptin 12.5 mg with metformin HCl 1000 mg, 1.8% in the metformin HCl 500 mg and 6.3% in the metformin HCl 1000 mg treatment groups.

In a 26 week placebo-controlled trial of alogliptin 25 mg administered once daily as add-on to metformin regimen, the number of patients reporting hypoglycemic events was 0% in the alogliptin co-administered with metformin HCl and 2.9% in the placebo treatment groups.

In a 52 week, active-controlled, double-blind trial of alogliptin once daily as add-on therapy to the combination of pioglitazone 30 mg and metformin compared to the titration of pioglitazone 30 mg to 45 mg and metformin, the number of patients reporting hypoglycemia was 4.5% in the alogliptin 25 mg with pioglitazone 30 mg and metformin group versus 1.5% in the pioglitazone 45 mg with metformin group.

In an interim analysis conducted in a 104 week, double-blind, active-controlled trial of alogliptin 25 mg in combination with metformin, the number of patients reporting hypoglycemia was 1.4% in the alogliptin 25 mg with metformin group versus 23.8% in the glipizide with metformin group.

Alogliptin

Hypoglycemic events were documented based upon a blood glucose value and/or clinical signs and symptoms of hypoglycemia.

In the monotherapy trial, the incidence of hypoglycemia was 1.5% in patients treated with alogliptin compared to 1.6% with placebo. The use of alogliptin as add-on therapy to glyburide or insulin did not increase the incidence of hypoglycemia compared to placebo. In a monotherapy trial comparing alogliptin to a sulfonylurea in elderly patients, the incidence of hypoglycemia was 5.4% with alogliptin compared to 26% with glipizide.

In the EXAMINE trial, the incidence of investigator reported hypoglycemia was 6.7% in patients receiving alogliptin and 6.5% in patients receiving placebo. Serious adverse reactions of hypoglycemia were reported in 0.8% of patients treated with alogliptin and in 0.6% of patients treated with placebo.

Metformin HCl

Table 3. Most Common Adverse Reactions (≥5%) in a Placebo-Controlled Clinical Trial of Metformin Monotherapy [Reactions that were more common in metformin than placebo-treated patients]
Adverse Reaction | Metformin Monotherapy (n=141) | Placebo (n=145)
Adverse Reaction | % of Patients
Diarrhea | 53.2 | 11.7
Nausea/vomiting | 25.5 | 8.3
Flatulence | 12.1 | 5.5
Asthenia | 9.2 | 5.5
Indigestion | 7.1 | 4.1
Abdominal discomfort | 6.4 | 4.8
Headache | 5.7 | 4.8

Laboratory Abnormalities

Alogliptin and Metformin HCl

No clinically meaningful differences were observed among treatment groups regarding hematology, serum chemistry or urinalysis results.

Metformin HCl

In metformin clinical trials of 29 week duration, a decrease to subnormal levels of previously normal serum vitamin B12 levels was observed in approximately 7% of patients.

6.2 Postmarketing Experience

The following adverse reactions have been identified during postmarketing use. Because these reactions are reported voluntarily from a population of uncertain size, it is not always possible to reliably estimate their frequency or establish a causal relationship to drug exposure.

Alogliptin

Gastrointestinal Disorders: acute pancreatitis, diarrhea, constipation, nausea, ileus

Hepatobiliary Disorders: fulminant hepatic failure

Immune System Disorders: hypersensitivity reactions including anaphylaxis

Investigations: hepatic enzyme elevations

Musculoskeletal and Connective Tissue Disorders: severe and disabling arthralgia, rhabdomyolysis

Renal and Urinary Disorders: tubulointerstitial nephritis

Skin and Subcutaneous Tissue Disorders: angioedema, rash, urticaria and severe cutaneous adverse reactions including Stevens-Johnson syndrome, bullous pemphigoid

Metformin

Hepatobiliary Disorders: Cholestatic, hepatocellular, mixed hepatocellular liver injury

7 DRUG INTERACTIONS

Metformin HCl

Carbonic Anhydrase Inhibitors
Clinical Impact: | Carbonic anhydrase inhibitors frequently cause a decrease in serum bicarbonate and induce non-anion gap, hyperchloremic metabolic acidosis. Concomitant use of these drugs with KAZANO may increase the risk of lactic acidosis.
Intervention: | Consider more frequent monitoring of these patients.
Examples: | Topiramate, zonisamide, acetazolamide or dichlorphenamide
Drugs that Reduce Metformin Clearance
Clinical Impact: | Concomitant use of drugs that interfere with common renal tubular transport systems involved in the renal elimination of metformin (e.g., organic cationic transporter-2 [OCT2]/multidrug and toxin extrusion [MATE] inhibitors) could increase systemic exposure to metformin and may increase the risk for lactic acidosis [see Clinical Pharmacology (12.3)].
Intervention: | Consider the benefits and risks of concomitant use.
Examples: | Ranolazine, vandetanib, dolutegravir, and cimetidine
Alcohol
Clinical Impact: | Alcohol is known to potentiate the effect of metformin on lactate metabolism.
Intervention: | Warn patients against excessive alcohol intake while receiving KAZANO.
Insulin Secretagogues and Insulin
Clinical Impact: | Coadministration of KAZANO with an insulin secretagogue (e.g., sulfonylurea) or with insulin may increase the risk of hypoglycemia.
Intervention: | Patients may require a lower dose of the insulin secretagogue or insulin.
Drugs Affecting Glycemic Control
Clinical Impact: | Certain drugs tend to produce hyperglycemia and may lead to loss of glycemic control.
Intervention: | When such drugs are administered to a patient receiving KAZANO, the patient should be closely observed for loss of blood glucose control. When such drugs are withdrawn from a patient receiving KAZANO, the patient should be observed closely for hypoglycemia.
Examples: | Thiazides and other diuretics, corticosteroids, phenothiazines, thyroid products, estrogens, oral contraceptives, phenytoin, nicotinic acid, sympathomimetics, calcium channel blocking drugs and isoniazid

Alogliptin

Cytochrome (CYP) P450, CYP-Substrates or Inhibitors
Clinical Impact: | Insulin Secretagogues and Insulin Insulin and insulin secretagogues are known to cause hypoglycemia. Coadministration of KAZANO with an insulin secretagogue (e.g., sulfonylurea) or insulin may require lower dosages of the insulin secretagogue or insulin to reduce the risk of hypoglycemia [see Warnings and Precautions (5.7)].

8 USE IN SPECIFIC POPULATIONS

8.1 Pregnancy

Risk Summary

Limited available data with KAZANO or alogliptin in pregnant women are not sufficient to inform a drug-associated risk for major birth defects and miscarriage. Published studies with metformin use during pregnancy have not reported a clear association with metformin and major birth defect or miscarriage risk [see Data]. There are risks to the mother and fetus associated with poorly controlled diabetes mellitus in pregnancy [see Clinical Considerations].

Concomitant administration of alogliptin and metformin in pregnant rats during the period of organogenesis did not cause adverse developmental effects in offspring at maternal exposures up to 28 times and two times the 25 mg and 2000 mg clinical doses, respectively [see Data].

The estimated background risk of major birth defects is 6-10% in women with pre-gestational diabetes mellitus with a HbA1c >7 and has been reported to be as high as 20-25% in women with HbA1c >10. The estimated background risk of miscarriage for the indicated population is unknown. In the U.S. general population, the estimated background risk of major defects and miscarriage in clinically recognized pregnancies is 2-4% and 15-20%, respectively.

Clinical Considerations

Disease-associated Maternal and/or Embryo/Fetal Risk

Poorly controlled diabetes mellitus in pregnancy increases the maternal risk for diabetic ketoacidosis, pre-eclampsia, spontaneous abortions, preterm delivery, and delivery complications. Poorly controlled diabetes mellitus increases the fetal risk for major malformations, still birth, and macrosomia related morbidity.

Data

Human Data

Published data from postmarketing studies do not report a clear association with metformin and major birth defects, miscarriage, or adverse maternal or fetal outcomes when metformin is used during pregnancy. However, these studies cannot definitely establish the absence of any metformin-associated risk because of methodological limitations, including small sample size and inconsistent comparator groups.

Animal Data

Alogliptin and Metformin

Concomitant administration of alogliptin and metformin in pregnant rats during the period of organogenesis did not cause adverse developmental effects in offspring at a dose of 100 mg/kg alogliptin and 150 mg/kg metformin, or approximately 28 and two times the clinical dose of alogliptin (25 mg) and metformin (2000 mg), respectively based on plasma drug exposure (AUC).

Alogliptin

Alogliptin administered to pregnant rabbits and rats during the period of organogenesis did not cause adverse developmental effects at doses of up to 200 mg/kg and 500 mg/kg, or 149 times and 180 times the 25 mg clinical dose, respectively, based on plasma drug exposure (AUC). Placental transfer of alogliptin into the fetus was observed following oral dosing to pregnant rats.

No adverse developmental outcomes were observed in offspring when alogliptin was administered to pregnant rats during gestation and lactation at doses up to 250 mg/kg (approximately 95 times the 25 mg clinical dose, based on AUC).

Metformin HCl

Metformin HCl did not cause adverse developmental effects when administered to pregnant Sprague Dawley rats and rabbits up to 600 mg/kg/day during the period of organogenesis. This represents an exposure of about two to six times a clinical dose of 2000 mg based on body surface area (mg/m^2) for rats and rabbits, respectively.

8.2 Lactation

Risk Summary

There is no information regarding the presence of KAZANO or alogliptin in human milk, the effects on the breastfed infant, or the effects on milk production. Alogliptin is present in rat milk. Limited published studies report that metformin is present in human milk [see Data]. However, there is insufficient information to determine the effects of metformin on the breastfed infant and no available information on the effects of metformin on milk production. The developmental and health benefits of breastfeeding should be considered along with the mother's clinical need for KAZANO and any potential adverse effects on the breastfed infant from KAZANO or from the underlying maternal condition.

Data

Published clinical lactation studies report that metformin is present in human milk which resulted in infant doses approximately 0.11% to 1% of the maternal weight-adjusted dosage and a milk/plasma ratio (based on AUC) ranging between 0.13 and 1. However, the studies were not designed to definitely establish the risk of use of metformin during lactation because of small sample size and limited adverse event data collected in infants.

8.3 Females and Males of Reproductive Potential

There is the potential for unintended pregnancy with premenopausal women as therapy with metformin may result in ovulation in some premenopausal anovulatory women.

8.4 Pediatric Use

The safety and effectiveness of KAZANO have not been established in pediatric patients.

Effectiveness of alogliptin was not demonstrated in a 52 week, randomized, double-blind, placebo-controlled trial (NCT02856113) in 151 pediatric patients aged 10 to 17 years with inadequately controlled type 2 diabetes mellitus.

8.5 Geriatric Use

Alogliptin and Metformin HCl

Elderly patients are more likely to have decreased renal function. Monitor renal function in the elderly more frequently [see Warnings and Precautions (5.1), Clinical Pharmacology (12.3)].

Of the total number of patients (N=2095) in clinical safety and efficacy trials, 343 (16.4%) patients were 65 years and older and 37 (1.8%) patients were 75 years and older. No overall differences in safety or effectiveness were observed between these patients and younger patients.

Alogliptin

Of the total number of patients (N=9052) in clinical safety and efficacy studies treated with alogliptin, 2,257 (24.9%) patients were 65 years and older and 386 (4.3%) patients were 75 years and older. No overall differences in safety or effectiveness were observed between patients 65 years and over and younger patients.

Metformin HCl

Controlled studies of metformin did not include sufficient numbers of subjects age 65 and over to determine whether they respond differently from younger patients. Other reported clinical experience has not identified differences in responses between the elderly and younger patients.

In general, dose selection for an elderly patient should be cautious, usually starting at the low end of the dosing range, reflecting the greater frequency of decreased hepatic, renal and cardiac function, and of concomitant disease or other drug therapy and the higher risk of lactic acidosis. Assess renal function more frequently in elderly patients [see Contraindications (4), Warnings and Precautions (5.1), Clinical Pharmacology (12.3)].

8.6 Renal Impairment

Metformin is substantially excreted by the kidney, and the risk of metformin accumulation and lactic acidosis increases with the degree of renal impairment. KAZANO is contraindicated in severe renal impairment, patients with an eGFR below 30 mL/min/1.73 m^2 [see Dosage and Administration (2.2), Contraindications (4), Warnings and Precautions (5.1), Clinical Pharmacology (12.3)].

8.7 Hepatic Impairment

Use of metformin in patients with hepatic impairment has been associated with some cases of lactic acidosis. KAZANO is not recommended in patients with hepatic impairment [see Warnings and Precautions (5.1)].

10 OVERDOSAGE

Overdose of metformin has occurred, including ingestion of amounts greater than 50 grams. Hypoglycemia was reported in approximately 10% of cases, but no causal association with metformin has been established. Lactic acidosis has been reported in approximately 32% of metformin overdose cases [see Warnings and Precautions (5.1)].

In the event of an overdose, it is reasonable to institute the necessary clinical monitoring and supportive therapy as dictated by the patient's clinical status. Per clinical judgment, it may be reasonable to initiate removal of unabsorbed material from the gastrointestinal tract.

Alogliptin is minimally dialyzable; over a three-hour hemodialysis session, approximately 7% of the drug was removed. Therefore, hemodialysis is unlikely to be beneficial in an overdose situation. It is not known if alogliptin is dialyzable by peritoneal dialysis.

Metformin is dialyzable with a clearance of up to 170 mL/min under good hemodynamic conditions. Hemodialysis may be useful for removal of accumulated drug from patients in whom metformin overdosage is suspected.

In the event of an overdose, contact the Poison Help Line, (1-800-222-1222) or a medical toxicologist for additional overdosage management recommendations.

11 DESCRIPTION

KAZANO tablets contain two oral antihyperglycemic drugs used in the management of type 2 diabetes mellitus: alogliptin and metformin HCl.

Alogliptin

Alogliptin is a selective, orally bioavailable inhibitor of the enzymatic activity of DPP-4. Chemically, alogliptin is prepared as a benzoate salt, which is identified as 2-({6-[(3R)-3-aminopiperidin-1-yl]-3-methyl-2,4-dioxo-3,4-dihydropyrimidin-1(2H)-yl}methyl)benzonitrile monobenzoate. It has a molecular formula of C18H21N5O2∙C7H6O2 and a molecular weight of 461.51 daltons; the structural formula is:

Alogliptin benzoate is a white to off-white crystalline powder containing one asymmetric carbon in the aminopiperidine moiety. It is soluble in dimethylsulfoxide, sparingly soluble in water and methanol, slightly soluble in ethanol and very slightly soluble in octanol and isopropyl acetate.

Metformin HCl

Metformin HCl (N,N-dimethylimidodicarbonimidic diamide HCl) is not chemically or pharmacologically related to any other classes of oral antihyperglycemic agents. Metformin HCl is a white to off-white crystalline compound with a molecular formula of C4H11N5∙HCl and a molecular weight of 165.63. Metformin HCl is freely soluble in water and is practically insoluble in acetone, ether and chloroform. The pKa of metformin is 12.4. The pH of a 1% aqueous solution of metformin HCl is 6.68. The structural formula is as shown:

KAZANO is available as a tablet for oral administration containing 17 mg alogliptin benzoate equivalent to 12.5 mg alogliptin and:

- 500 mg metformin HCl which is equivalent to 389.93 mg metformin base (12.5 mg/500 mg) or
- 1000 mg metformin HCl which is equivalent to 779.86 mg metformin base (12.5 mg/1000 mg).

KAZANO tablets contain the following inactive ingredients: crospovidone, magnesium stearate, mannitol, microcrystalline cellulose, and povidone; the tablets are film-coated with ferric oxide yellow, hypromellose 2910, talc, and titanium dioxide.

12 CLINICAL PHARMACOLOGY

12.1 Mechanism of Action

Alogliptin and Metformin HCl

KAZANO combines two antihyperglycemic agents with complementary and distinct mechanisms of action to improve glycemic control in patients with type 2 diabetes mellitus: alogliptin, a selective inhibitor of DPP-4, and metformin HCl, a member of the biguanide class.

Alogliptin

Increased concentrations of the incretin hormones such as glucagon-like peptide-1 (GLP-1) and glucose-dependent insulinotropic polypeptide (GIP) are released into the bloodstream from the small intestine in response to meals. These hormones cause insulin release from the pancreatic beta cells in a glucose-dependent manner but are inactivated by the DPP-4 enzyme within minutes. GLP-1 also lowers glucagon secretion from pancreatic alpha cells, reducing hepatic glucose production. In patients with type 2 diabetes mellitus, concentrations of GLP-1 are reduced but the insulin response to GLP-1 is preserved. Alogliptin is a DPP-4 inhibitor that slows the inactivation of the incretin hormones, thereby increasing their bloodstream concentrations and reducing fasting and postprandial glucose concentrations in a glucose-dependent manner in patients with type 2 diabetes mellitus. Alogliptin selectively binds to and inhibits DPP-4 but not DPP-8 or DPP-9 activity in vitro at concentrations approximating therapeutic exposures.

Metformin HCl

Metformin is a biguanide that improves glucose tolerance in patients with type 2 diabetes mellitus, lowering both basal and postprandial plasma glucose. Metformin decreases hepatic glucose production, decreases intestinal absorption of glucose and improves insulin sensitivity by increasing peripheral glucose uptake and utilization. With metformin therapy, insulin secretion remains unchanged while fasting insulin levels and daylong plasma insulin response may actually decrease.

12.2 Pharmacodynamics

Dose-Response Relationships

Alogliptin

Single-dose administration of alogliptin to healthy subjects resulted in a peak inhibition of DPP-4 within two to three hours after dosing. The peak inhibition of DPP-4 exceeded 93% across doses of 12.5 mg to 800 mg. Inhibition of DPP-4 remained above 80% at 24 hours for doses greater than or equal to 25 mg. Peak and total exposure over 24 hours to active GLP-1 were three- to four-fold greater with alogliptin (at doses of 25 to 200 mg) than placebo. In a 16 week, double-blind, placebo-controlled study, alogliptin 25 mg demonstrated decreases in postprandial glucagon while increasing postprandial active GLP-1 levels compared to placebo over an eight hour period following a standardized meal. It is unclear how these findings relate to changes in overall glycemic control in patients with type 2 diabetes mellitus. In this study, alogliptin 25 mg demonstrated decreases in two-hour postprandial glucose compared to placebo (-30 mg/dL versus 17 mg/dL, respectively).

Multiple-dose administration of alogliptin to patients with type 2 diabetes mellitus also resulted in a peak inhibition of DPP-4 within one to two hours and exceeded 93% across all doses (25 mg, 100 mg and 400 mg) after a single dose and after 14 days of once-daily dosing. At these doses of alogliptin, inhibition of DPP-4 remained above 81% at 24 hours after 14 days of dosing.

Cardiac Electrophysiology

Alogliptin

In a randomized, placebo-controlled, four-arm, parallel-group study, 257 subjects were administered either alogliptin 50 mg, alogliptin 400 mg, moxifloxacin 400 mg or placebo once daily for a total of seven days. No increase in corrected QT (QTc) was observed with either dose of alogliptin. At the 400 mg dose, peak alogliptin plasma concentrations were 19-fold higher than the peak concentrations following the maximum recommended clinical dose of 25 mg.

12.3 Pharmacokinetics

Absorption

Alogliptin and Metformin HCl

There is no clinically meaningful difference in PK exposures (AUC and Cmax) of alogliptin and metformin when taken a single dose of the combination tablet and individual alogliptin and metformin tablets taken concomitantly.

Alogliptin

After administration of single, oral doses up to 800 mg in healthy subjects, the peak plasma alogliptin concentration (median Tmax) occurred one to two hours after dosing. The absolute bioavailability of alogliptin is approximately 100%.

Metformin HCl

Studies using single oral doses of metformin HCl tablets 500 mg to 1500 mg and 850 mg to 2550 mg indicate that there is a lack of dose proportionality with increasing doses, which is due to decreased absorption rather than an alteration in elimination. The absolute bioavailability of metformin following administration of a 500 mg metformin HCl tablet given under fasting conditions is approximately 50% to 60%.

Effect of Food

Alogliptin and Metformin HCl

Administration of KAZANO with food resulted in no change in total exposure (AUC) of alogliptin and metformin. Mean peak plasma concentrations of alogliptin and metformin were decreased by 13% and 28%, respectively, when administered with food. There was no change in time to peak plasma concentrations (Tmax) for alogliptin under fed conditions, however, there was a delayed Tmax for metformin of 1.5 hours. These changes are not likely to be clinically significant.

Alogliptin

Administration of alogliptin with a high-fat meal results in no significant change in total and peak exposure to alogliptin.

Metformin HCl

Food decreases the extent of and slightly delays the absorption of metformin, as shown by approximately a 40% lower mean peak plasma concentration (Cmax), a 25% lower area under the plasma concentration versus time curve (AUC), and a 35-minute prolongation of time to peak plasma concentration (Tmax) following administration of a single 850 mg tablet of metformin HCl with food compared to the same tablet strength administered fasting. The clinical relevance of these decreases is unknown.

Distribution

Alogliptin

Following a single, 12.5 mg intravenous infusion of alogliptin to healthy subjects, the volume of distribution during the terminal phase was 417 L, indicating that the drug is well distributed into tissues.

Alogliptin is 20% bound to plasma proteins.

Metformin HCl

The apparent volume of distribution (V/F) of metformin following single oral doses of immediate release metformin HCl tablets 850 mg averaged 654 ± 358 L. Metformin is negligibly bound to plasma proteins. Metformin partitions into erythrocytes, most likely as a function of time.

Elimination

Alogliptin

Alogliptin was eliminated with a mean terminal half-life (t1/2) of approximately 21 hours. The renal clearance of alogliptin (9.6 L/hr) indicates some active renal tubular secretion and systemic clearance was 14.0 L/hr.

Metformin HCl

In blood, the elimination half-life is approximately 17.6 hours, suggesting that the erythrocyte mass may be a compartment of distribution. The plasma elimination half-life is approximately 6.2 hours. Renal clearance is approximately 3.5 times greater than creatinine clearance, which indicates that tubular secretion is the major route of metformin excretion.

Metabolism

Alogliptin

Alogliptin does not undergo extensive metabolism and 60% to 71% of the dose is excreted as unchanged drug in the urine.

Two minor metabolites were detected following administration of an oral dose of [^14C] alogliptin, N-demethylated, M-I (less than 1% of the parent compound), and N-acetylated alogliptin, M-II (less than 6% of the parent compound). M-I is an active metabolite and is an inhibitor of DPP-4 similar to the parent molecule; M-II does not display any inhibitory activity toward DPP-4 or other DPP-related enzymes. In vitro data indicate that CYP2D6 and CYP3A4 contribute to the limited metabolism of alogliptin.

Alogliptin exists predominantly as the (R)-enantiomer (more than 99%) and undergoes little or no chiral conversion in vivo to the (S)-enantiomer. The (S)-enantiomer is not detectable at the 25 mg dose.

Metformin HCl

Intravenous single-dose studies in healthy subjects demonstrate that metformin is excreted unchanged in the urine and does not undergo hepatic metabolism (no metabolites have been identified in humans) or biliary excretion.

Excretion

Alogliptin

The primary route of elimination of [^14C] alogliptin-derived radioactivity occurs via renal excretion (76%) with 13% recovered in the feces, achieving a total recovery of 89% of the administered radioactive dose.

Metformin HCl

Following oral administration, approximately 90% of the absorbed drug is eliminated via the renal route within the first 24 hours.

Specific Populations

Geriatric Patients

Due to declining renal function in the elderly, measurement of creatinine clearance should be obtained prior to initiation of therapy.

Alogliptin

Age (18 to 80 years old) did not have any clinically meaningful effect on the pharmacokinetics of alogliptin.

Metformin HCl

Limited data from controlled pharmacokinetic studies of metformin in healthy elderly subjects suggest that total plasma clearance of metformin is decreased, the half-life is prolonged, and Cmax is increased, compared to healthy young subjects. From these data it appears that the change in metformin pharmacokinetics with aging is primarily accounted for by a change in renal function.

Male and Female Patients

Alogliptin

Gender did not have any clinically meaningful effect on the pharmacokinetics of alogliptin.

Metformin HCl

Metformin pharmacokinetic parameters did not differ significantly between normal subjects and patients with type 2 diabetes mellitus when analyzed according to gender. Similarly, in controlled clinical studies in patients with type 2 diabetes mellitus, the antihyperglycemic effect of metformin HCl tablets was comparable in males and females.

Racial or Ethnic Groups

Alogliptin

Race (White, Black or African American and Asian) did not have any clinically meaningful effect on the pharmacokinetics of alogliptin.

Metformin HCl

No studies of metformin pharmacokinetic parameters according to race have been performed. In controlled clinical studies of metformin in patients with type 2 diabetes mellitus, the antihyperglycemic effect was comparable in Whites (n=249), Blacks or Africans Americans (n=51) and Hispanics or Latino (n=24).

Patients with Renal Impairment

Metformin HCl

In patients with decreased renal function (based on measured creatine clearance), the plasma and blood half-life of metformin is prolonged and the renal clearance is decreased [see Contraindications (4), Warnings and Precautions (5.1)].

Patients with Hepatic Impairment

Alogliptin

Total exposure to alogliptin was approximately 10% lower and peak exposure was approximately 8% lower in patients with moderate hepatic impairment (Child-Pugh Grade B) compared to healthy subjects. The magnitude of these reductions is not considered to be clinically meaningful. Patients with severe hepatic impairment (Child-Pugh Grade C) have not been studied.

Metformin HCl

No pharmacokinetic studies of metformin have been conducted in subjects with hepatic impairment.

Drug Interaction Studies

Alogliptin and Metformin HCl

Administration of alogliptin 100 mg once daily with metformin HCl 1000 mg twice daily for six days had no meaningful effect on the pharmacokinetics of alogliptin or metformin.

Specific pharmacokinetic drug interaction studies with KAZANO have not been performed, although such studies have been conducted with the individual components of KAZANO (alogliptin and metformin).

Alogliptin

Clinical Studies

In Vivo Assessment of Drug Interactions

Effects of Alogliptin on the Pharmacokinetics of Other Drugs

In clinical studies, alogliptin did not meaningfully increase the systemic exposure to the following drugs that are metabolized by CYP isozymes or excreted unchanged in urine (Figure 1). No dose adjustment of alogliptin is recommended based on results of the described pharmacokinetic studies.

Figure 1. Effect of Alogliptin on the Pharmacokinetic Exposure to Other Drugs

* Warfarin was given once daily at a stable dose in the range of 1 mg to 10 mg. Alogliptin had no significant effect on the prothrombin time (PT) or International Normalized Ratio (INR).

** Caffeine (1A2 substrate), tolbutamide (2C9 substrate), dextromethorphan (2D6 substrate), midazolam (3A4 substrate) and fexofenadine (P-gp substrate) were administered as a cocktail.

Effects of Other Drugs on the Pharmacokinetics of Alogliptin

There are no clinically meaningful changes in the pharmacokinetics of alogliptin when alogliptin is administered concomitantly with the drugs described below (Figure 2).

Figure 2. Effect of Other Drugs on the Pharmacokinetic Exposure of Alogliptin

Metformin HCl

Pharmacokinetic drug interaction studies have been performed on metformin (Tables 4 and 5).

Table 4. Effect of Coadministered Drug on Plasma Metformin Systemic Exposure
Coadministered Drug | Dose of Coadministered Drug [All metformin and coadministered drugs were given as single doses] | Dose of Metformin HCl | Geometric Mean Ratio (ratio with/without coadministered drug) No effect = 1.00
Coadministered Drug | Dose of Coadministered Drug [All metformin and coadministered drugs were given as single doses] | Dose of Metformin HCl | AUC [AUC = AUC0˗∞] | Cmax
No dosing adjustments required for the following:
Glyburide | 5 mg | 500 mg [Metformin HCl extended-release tablets 500 mg] | 0.98 [Ratio of arithmetic means] | 0.99
Furosemide | 40 mg | 850 mg | 1.09 | 1.22
Nifedipine | 10 mg | 850 mg | 1.16 | 1.21
Propranolol | 40 mg | 850 mg | 0.90 | 0.94
Ibuprofen | 400 mg | 850 mg | 1.05 | 1.07
Drugs that are eliminated by renal tubular secretion may increase the accumulation of metformin [see Warnings and Precautions (5), Drug Interactions (7)].
Cimetidine | 400 mg | 850 mg | 1.40 | 1.61
Carbonic anhydrase inhibitors may cause metabolic acidosis [see Warnings and Precautions (5), Drug Interactions (7)].
Topiramate | 100 mg [At steady-state with topiramate 100 mg every 12 hours and metformin 500 mg every 12 hours; AUC = AUC0-12h] | 500 mg | 1.25 | 1.17

Table 5. Effect of Metformin on Coadministered Drug Systemic Exposure
Coadministered Drug | Dose of Coadministered Drug [All metformin and coadministered drugs were given as single doses] | Dose of Metformin HCl | Geometric Mean Ratio (ratio with/without coadministered drug) No effect = 1.00
Coadministered Drug | Dose of Coadministered Drug [All metformin and coadministered drugs were given as single doses] | Dose of Metformin HCl | AUC [AUC = AUC0˗∞] | Cmax
No dosing adjustments required for the following:
Glyburide | 5 mg | 500 mg [AUC0-24 hr reported] | 0.78 [Ratio of arithmetic means, p-value of difference <0.05] | 0.63
Furosemide | 40 mg | 850 mg | 0.87 | 0.69
Nifedipine | 10 mg | 850 mg | 1.10 | 1.08
Propranolol | 40 mg | 850 mg | 1.01 | 0.94
Ibuprofen | 400 mg | 850 mg | 0.97 [Ratio of arithmetic means] | 1.01
Cimetidine | 400 mg | 850 mg | 0.95 | 1.01

13 NONCLINICAL TOXICOLOGY

13.1 Carcinogenesis, Mutagenesis, Impairment of Fertility

Alogliptin and Metformin HCl

No carcinogenicity, mutagenicity or impairment of fertility studies have been conducted with KAZANO. The following data are based on findings in studies performed with alogliptin or metformin individually.

Alogliptin

Rats were administered oral doses of 75, 400 and 800 mg/kg alogliptin for two years. No drug-related tumors were observed up to 75 mg/kg or approximately 32 times the maximum recommended clinical dose of 25 mg, based on area under the plasma concentration curve (AUC) exposure. At higher doses (approximately 308 times the maximum recommended clinical dose of 25 mg), a combination of thyroid C-cell adenomas and carcinomas increased in male but not female rats. No drug-related tumors were observed in mice after administration of 50, 150 or 300 mg/kg alogliptin for two years, or up to approximately 51 times the maximum recommended clinical dose of 25 mg, based on AUC exposure.

Alogliptin was not mutagenic or clastogenic, with and without metabolic activation, in the Ames test with S. typhimurium and E. coli or the cytogenetic assay in mouse lymphoma cells. Alogliptin was negative in the in vivo mouse micronucleus study.

In a fertility study in rats, alogliptin had no adverse effects on early embryonic development, mating or fertility, at doses up to 500 mg/kg, or approximately 172 times the clinical dose based on plasma drug exposure (AUC).

Metformin HCl

Long-term carcinogenicity studies have been performed in rats (dosing duration of 104 weeks) and mice (dosing duration of 91 weeks) at doses up to and including 900 mg/kg and 1500 mg/kg, respectively. These doses are both approximately four times the maximum recommended human daily dose of 2000 mg based on body surface area comparisons. No evidence of carcinogenicity with metformin was found in either male or female mice. Similarly, there was no tumorigenic potential observed with metformin in male rats. There was an increased incidence of benign stromal uterine polyps in female rats treated with 900 mg/kg.

There was no evidence of a mutagenic potential of metformin in the following in vitro tests: Ames test (S. typhimurium), gene mutation test (mouse lymphoma cells) or chromosomal aberrations test (human lymphocytes). Results in the in vivo mouse micronucleus test were also negative.

Fertility of male or female rats was unaffected by metformin when administered at doses as high as 600 mg/kg, which is approximately three times the maximum recommended human daily dose based on body surface area comparisons.

14 CLINICAL STUDIES

14.1 Overview of Clinical Trials in Adults with Type 2 Diabetes Mellitus

The coadministration of alogliptin and metformin has been studied in patients with type 2 diabetes mellitus inadequately controlled on either diet and exercise alone, on metformin alone or metformin in combination with a thiazolidinedione.

A total of 2,114 patients with type 2 diabetes mellitus were randomized in three double-blind, placebo- or active-controlled clinical safety and efficacy trials conducted to evaluate the effects of alogliptin co-administered with metformin HCl on glycemic control. Among those, 2,095 patients were exposed to the trial medication. The racial distribution of patients exposed to trial medication was 69% White, 16% Asian, 7% Black or African American, 2% American Indian or Alaska Native, 0% Native Hawaiian/Other Pacific Islander and 6% Multiracial or other racial groups. The ethnic distribution was 24% Hispanic or Latino. Patients had an overall mean age of approximately 54.4 years (range 22 to 80 years). In patients with type 2 diabetes mellitus, treatment with alogliptin co-administered with metformin HCl produced clinically meaningful and statistically significant improvements in A1C versus comparator. As is typical for trials of agents to treat type 2 diabetes mellitus, the mean reduction in hemoglobin A1c (A1C) with alogliptin co-administered with metformin HCl appears to be related to the degree of A1C elevation at baseline.

14.2 Alogliptin and Metformin Coadministration in Patients with Type 2 Diabetes Mellitus Inadequately Controlled on Diet and Exercise

In a 26 week, double-blind, placebo-controlled trial, a total of 784 patients inadequately controlled on diet and exercise alone (mean baseline A1C = 8.4%) were randomized to one of seven treatment groups: placebo; metformin HCl 500 mg or metformin HCl 1000 mg twice daily, alogliptin 12.5 mg twice daily, or alogliptin 25 mg daily; alogliptin 12.5 mg in combination with metformin HCl 500 mg or metformin HCl 1000 mg twice daily. Both coadministration treatment arms (alogliptin 12.5 mg + metformin HCl 500 mg and alogliptin 12.5 mg + metformin HCl 1000 mg) resulted in significant improvements in A1C (Figure 3) and FPG when compared with their respective individual alogliptin and metformin component regimens (Table 6). Coadministration treatment arms demonstrated improvements in two-hour postprandial glucose (PPG) compared to alogliptin alone or metformin alone (Table 6). A total of 12% of patients receiving alogliptin 12.5 mg + metformin HCl 500 mg, 3% of patients receiving alogliptin 12.5 mg + metformin HCl 1000 mg, 17% of patients receiving alogliptin 12.5 mg, 23% of patients receiving metformin HCl 500 mg, 11% of patients receiving metformin HCl 1000 mg and 39% of patients receiving placebo required glycemic rescue.

Improvements in A1C were not affected by gender, age, race or baseline BMI. The mean decrease in body weight was similar between metformin alone and alogliptin when co-administered with metformin HCl. Lipid effects were neutral.

Table 6. Glycemic Parameters at Week 26 for Alogliptin and Metformin HCl Alone and in Combination in Patients with Type 2 Diabetes Mellitus
 | Placebo | Alogliptin 12.5 mg twice daily | Metformin HCl 500 mg twice daily | Metformin HCl 1000 mg twice daily | Alogliptin 12.5 mg + Metformin HCl 500 mg twice daily | Alogliptin 12.5 mg + Metformin HCl 1000 mg twice daily
A1C (%) [Intent-to-treat population using last observation on trial prior to discontinuation of double-blind trial medication or sulfonylurea rescue therapy for patients needing rescue] | N=102 | N=104 | N=103 | N=108 | N=102 | N=111
Baseline (mean) | 8.5 | 8.4 | 8.5 | 8.4 | 8.5 | 8.4
Change from baseline (adjusted mean [Least squares means adjusted for treatment, geographic region and baseline value]) | 0.1 | -0.6 | -0.7 | -1.1 | -1.2 | -1.6
Difference from metformin (adjusted mean with 95% confidence interval) | - | - | - | - | -0.6 [p<0.05 when compared to metformin and alogliptin alone] (-0.9, -0.3) | -0.4 (-0.7, -0.2)
Difference from alogliptin (adjusted mean with 95% confidence interval) | - | - | - | - | -0.7 (-1.0, -0.4) | -1.0 (-1.3, -0.7)
% of Patients (n/N) achieving A1C <7% [Compared using logistic regression] | 4% (4/102) | 20% (21/104) | 27% (28/103) | 34% (37/108) | 47% (48/102) | 59% (66/111)
FPG (mg/dL) | N=105 | N=106 | N=106 | N=110 | N=106 | N=112
Baseline (mean) | 187 | 177 | 180 | 181 | 176 | 185
Change from baseline (adjusted mean) | 12 | -10 | -12 | -32 | -32 | -46
Difference from metformin (adjusted mean with 95% confidence interval) | - | - | - | - | -20 (-33, -8) | -14 (-26, -2)
Difference from alogliptin (adjusted mean with 95% confidence interval) | - | - | - | - | -22 (-35, -10) | -36 (-49, -24)
2-Hour PPG (mg/dL) [Intent-to-treat population using data available at Week 26] | N=26 | N=34 | N=28 | N=37 | N=31 | N=37
Baseline (mean) | 263 | 272 | 247 | 266 | 261 | 268
Change from baseline (adjusted mean) | -21 | -43 | -49 | -54 | -68 | -86
Difference from metformin (adjusted mean with 95% confidence interval) | - | - | - | - | -19 (-49, 11) | -32 (-58, -5)
Difference from alogliptin (adjusted mean with 95% confidence interval) | - | - | - | - | -25 (-53, 3) | -43 (-70, -16)

Figure 3. Change from Baseline A1C at Week 26 with Alogliptin and Metformin Alone and Alogliptin in Combination with Metformin

14.3 Alogliptin and Metformin Coadministration in Patients with Type 2 Diabetes Mellitus Inadequately Controlled on Metformin Alone

In a 26 week, double-blind, placebo-controlled trial, a total of 527 patients already on metformin (mean baseline A1C = 8%) were randomized to receive alogliptin 12.5 mg, alogliptin 25 mg, or placebo once daily. Patients were maintained on a stable dose of metformin HCl (median daily dose = 1700 mg) during the treatment period. Alogliptin 25 mg in combination with metformin resulted in statistically significant improvements from baseline in A1C and FPG at Week 26, when compared to placebo (Table 7). A total of 8% of patients receiving alogliptin 25 mg and 24% of patients receiving placebo required glycemic rescue. Improvements in A1C were not affected by gender, age, race, baseline BMI or baseline metformin dose.

The mean decrease in body weight was similar between alogliptin 25 mg and placebo when given in combination with metformin. Lipid effects were also neutral.

Table 7. Glycemic Parameters at Week 26 in a Placebo-Controlled Trial of Alogliptin as Add-on Therapy to Metformin in Adults with Type 2 Diabetes Mellitus [Intent-to-treat population using last observation on trial]
 | Alogliptin 25 mg + Metformin | Placebo + Metformin
A1C (%) | N=203 | N=103
Baseline (mean) | 7.9 | 8.0
Change from baseline (adjusted mean [Least squares means adjusted for treatment, baseline value, geographic region and baseline metformin dose]) | -0.6 | -0.1
Difference from placebo (adjusted mean with 95% confidence interval) | -0.5 [p<0.001 compared to placebo] (-0.7, -0.3) | ˗
% of patients (n/N) achieving A1C ≤7% | 44% (92/207) | 18% (19/104)
FPG (mg/dL) | N=204 | N=104
Baseline (mean) | 172 | 180
Change from baseline (adjusted mean) | -17 | 0
Difference from placebo (adjusted mean with 95% confidence interval) | -17 (-26, -9) | ˗

14.4 Alogliptin Add-On Therapy in Patients with Type 2 Diabetes Mellitus Inadequately Controlled on the Combination of Metformin and Pioglitazone

In a 52 week, active-comparator trial, a total of 803 patients inadequately controlled (mean baseline A1C = 8.2%) on a current regimen of pioglitazone 30 mg and metformin were randomized to either receive the addition of once-daily alogliptin 25 mg or the titration of pioglitazone 30 mg to 45 mg following a four week single-blind, placebo run-in period. Patients were maintained on a stable dose of metformin HCl (median daily dose = 1700 mg). Patients who failed to meet prespecified hyperglycemic goals during the 52 week treatment period received glycemic rescue therapy.

In combination with pioglitazone and metformin, alogliptin 25 mg was shown to be statistically superior in lowering A1C and FPG compared with the titration of pioglitazone from 30 to 45 mg at Week 26 and at Week 52 (Table 8). A total of 11% of patients in the alogliptin 25 mg in combination with pioglitazone 30 mg and metformin treatment group and 22% of patients in the up titration of pioglitazone in combination with metformin treatment group required glycemic rescue. Improvements in A1C were not affected by gender, age, race or baseline BMI.

The mean increase in body weight was similar in both treatment arms. Lipid effects were neutral.

Table 8. Glycemic Parameters at Week 52 in an Active-Controlled Trial of Alogliptin as Add-On Combination Therapy to Metformin and Pioglitazone in Adults with Type 2 Diabetes Mellitus [Intent-to-treat population using last observation on trial]
 | Alogliptin 25 mg + Pioglitazone 30 mg + Metformin | Pioglitazone 45 mg + Metformin
A1C (%) | N=397 | N=394
Baseline (mean) | 8.2 | 8.1
Change from baseline (adjusted mean [Least squares means adjusted for treatment, baseline value, geographic region and baseline metformin dose]) | -0.7 | -0.3
Difference from pioglitazone 45 mg + metformin (adjusted mean with 95% confidence interval) | -0.4 [Noninferior and statistically superior to metformin + pioglitazone at the 0.025 one-sided significance level] (-0.5, -0.3) | -
% of Patients (n/N) achieving A1C ≤7% | 33% (134/404) [p<0.001 compared to pioglitazone 45 mg + metformin] | 21% (85/399)
Fasting Plasma Glucose (mg/dL) | N=399 | N=396
Baseline (mean) | 162 | 162
Change from baseline (adjusted mean) | -15 | -4
Difference from pioglitazone 45 mg + metformin (adjusted mean with 95% confidence interval) | -11 (-16, -6) | -

14.5 Cardiovascular Safety Trial

A randomized, double-blind, placebo-controlled cardiovascular outcomes trial (EXAMINE) was conducted to evaluate the cardiovascular risk of alogliptin. The trial compared the risk of major adverse cardiovascular events (MACE) between alogliptin (N=2701) and placebo (N=2679) when added to standard of care therapies for diabetes mellitus and atherosclerotic vascular disease (ASCVD). The trial was event driven and patients were followed until a sufficient number of primary outcome events accrued.

Eligible patients were adults with type 2 diabetes mellitus who had inadequate glycemic control at baseline (e.g., HbA1c >6.5%) and had been hospitalized for an acute coronary syndrome event (e.g., acute myocardial infarction or unstable angina requiring hospitalization) 15 to 90 days prior to randomization. The dose of alogliptin was based on estimated renal function at baseline per dosage and administration recommendations. The average time between an acute coronary syndrome event and randomization was approximately 48 days.

The mean age of the population was 61 years. Most patients were male (68%), White (73%), and were recruited from outside of the United States (86%). Asian and Black or African American patients contributed 20% and 4% of the total population, respectively. At the time of randomization patients had a diagnosis of type 2 diabetes mellitus for approximately 9 years, 87% had a prior myocardial infarction and 14% were current smokers. Hypertension (83%) and renal impairment (27% with an eGFR ≤60 mL/min/1.73 m^2) were prevalent co-morbid conditions. Use of medications to treat diabetes mellitus (e.g., metformin 73%, sulfonylurea 54%, insulin 41%), and ASCVD (e.g., statin 94%, aspirin 93%, renin-angiotensin system blocker 88%, beta-blocker 87%) was similar between patients randomized to alogliptin and placebo at baseline. During the trial, medications to treat diabetes mellitus and ASCVD could be adjusted to ensure care for these conditions adhered to standard of care recommendations set by local practice guidelines.

The primary endpoint in EXAMINE was the time to first occurrence of a MACE defined as the composite of cardiovascular death, nonfatal myocardial infarction (MI), or nonfatal stroke. The trial was designed to exclude a pre-specified risk margin of 1.3 for the hazard ratio of MACE. The median exposure to trial drug was 526 days and 95% of the patients were followed to trial completion or death.

Table 9 shows the trial results for the primary MACE composite endpoint and the contribution of each component to the primary MACE endpoint. The upper bound of the confidence interval was 1.16 and excluded a risk margin larger than 1.3.

Table 9. Patients with MACE in EXAMINE
Composite of first event of CV death, nonfatal MI or nonfatal stroke (MACE) | Alogliptin |  | Placebo |  | Hazard Ratio
Composite of first event of CV death, nonfatal MI or nonfatal stroke (MACE) | Number of Patients (%) | Rate per 100 PY [Patient Years (PY)] | Number of Patients (%) | Rate per 100 PY | (98% CI)
Composite of first event of CV death, nonfatal MI or nonfatal stroke (MACE) | N=2701 |  | N=2679
Composite of first event of CV death, nonfatal MI or nonfatal stroke (MACE) | 305 (11.3) | 7.6 | 316 (11.8) | 7.9 | 0.96 (0.80, 1.16)
CV Death | 89 (3.3) | 2.2 | 111 (4.1) | 2.8
Non-fatal MI | 187 (6.9) | 4.6 | 173 (6.5) | 4.3
Non-fatal stroke | 29 (1.1) | 0.7 | 32 (1.2) | 0.8

The Kaplan-Meier based cumulative event probability is presented in Figure 4 for the time to first occurrence of the primary MACE composite endpoint by treatment arm. The curves for placebo and alogliptin overlap throughout the duration of the trial. The observed incidence of MACE was highest within the first 60 days after randomization in both treatment arms (14.8 MACE per 100 PY), decreased from day 60 to the end of the first year (8.4 per 100 PY) and was lowest after 1 year of follow-up (5.2 per 100 PY).

Figure 4. Observed Cumulative Rate of MACE in EXAMINE

The rate of all cause death was similar between treatment arms with 153 (3.6 per 100 PY) recorded among patients randomized to alogliptin and 173 (4.1 per 100 PY) among patients randomized to placebo. A total of 112 deaths (2.9 per 100 PY) among patients on alogliptin and 130 among patients on placebo (3.5 per 100 PY) were adjudicated as cardiovascular deaths.

16 HOW SUPPLIED/STORAGE AND HANDLING

KAZANO tablets are available in the following strengths and packages:

12.5 mg/500 mg tablet: pale yellow, oblong, film-coated tablets with "12.5/500" debossed on one side and "322M" debossed on the other side, available in:

NDC 64764-335-60 | Bottles of 60 tablets
NDC 64764-335-80 | Bottles of 180 tablets
NDC 64764-335-77 | Bottles of 500 tablets

12.5 mg/1000 mg tablet: pale yellow, oblong, film-coated tablets with "12.5/1000" debossed on one side and "322M" debossed on the other side, available in:

NDC 64764-337-60 | Bottles of 60 tablets
NDC 64764-337-80 | Bottles of 180 tablets
NDC 64764-337-77 | Bottles of 500 tablets

STORAGE AND HANDLING

Store at 25°C (77°F); excursions permitted to 15° to 30°C (59° to 86°F) [see USP Controlled Room Temperature]. Keep container tightly closed.

17 PATIENT COUNSELING INFORMATION

Advise the patient to read the FDA-approved patient labeling (Medication Guide).

Lactic Acidosis

Explain the risks of lactic acidosis, its symptoms, and conditions that predispose to its development. Advise patients to discontinue KAZANO immediately and to promptly notify their healthcare provider if unexplained hyperventilation, myalgias, malaise, unusual somnolence or other nonspecific symptoms occur. Counsel patients against excessive alcohol intake and inform patients about importance of regular testing of renal function while receiving KAZANO. Instruct patients to inform their doctor that they are taking KAZANO prior to any surgical or radiological procedure, as temporary discontinuation may be required [see Warnings and Precautions (5.1)].

Pancreatitis

Inform patients that acute pancreatitis has been reported during use of alogliptin. Educate patients that persistent, severe abdominal pain, sometimes radiating to the back, which may or may not be accompanied by vomiting, is the hallmark symptom of acute pancreatitis. Instruct patients to promptly discontinue KAZANO and contact their physician if persistent severe abdominal pain occurs [see Warnings and Precautions (5.2)].

Heart Failure

Inform patients of the signs and symptoms of heart failure. Before initiating KAZANO, patients should be asked about a history of heart failure or other risk factors for heart failure including moderate to severe renal impairment. Instruct patients to contact their healthcare providers as soon as possible if they experience symptoms of heart failure, including increasing shortness of breath, rapid increase in weight, or swelling of the feet [see Warnings and Precautions (5.3)].

Hypersensitivity Reactions

Inform patients that allergic reactions have been reported during use of alogliptin and metformin. Instruct patients if symptoms of allergic reactions (including skin rash, hives and swelling of the face, lips, tongue and throat that may cause difficulty in breathing or swallowing) occur, patients should discontinue KAZANO and seek medical advice promptly [see Warnings and Precautions (5.4)].

Hepatic Effects

Inform patients that postmarketing reports of liver injury, sometimes fatal, have been reported during use of alogliptin. Instruct patients that if signs or symptoms of liver injury occur, patients should be instructed to discontinue KAZANO and seek medical advice promptly [see Warnings and Precautions (5.5)].

Vitamin B12 Levels

Inform patients about importance of regular hematological parameters while receiving metformin [see Warnings and Precautions (5.6)].

Hypoglycemia with Concomitant Use with Insulin or Insulin Secretagogues

Inform patients that hypoglycemia can occur, particularly when an insulin secretagogue or insulin is used in combination with KAZANO. Educate patients about the risks, symptoms and appropriate management of hypoglycemia [see Warnings and Precautions (5.7)].

Severe and Disabling Arthralgia

Inform patients that severe and disabling joint pain may occur with this class of drugs. The time to onset of symptoms can range from one day to years. Instruct patients to seek medical advice if severe joint pain occurs [see Warnings and Precautions (5.8)].

Bullous Pemphigoid

Inform patients that bullous pemphigoid may occur with this class of drugs. Instruct patients to seek medical advice if blisters or erosions occur [see Warnings and Precautions (5.9)].

Dosage

Instruct patients to take KAZANO only as prescribed twice daily and that it should be taken with food. Instruct patients if a dose is missed, not to double their next dose. Instruct patients that the tablets must never be split.

Females of Reproductive Age

Inform female patients that treatment with metformin may result in an unintended pregnancy in some premenopausal anovulatory females due to its effects on ovulation [see Use in Specific Populations (8.3)].

ALM143 R15

MEDICATION GUIDE
KAZANO® [Kah-ZAHN-oh]
(alogliptin and metformin HCl)
tablets

Read this Medication Guide carefully before you start taking KAZANO and each time you get a refill. There may be new information. This information does not take the place of talking with your doctor about your medical condition or treatment. If you have any questions about KAZANO, ask your doctor or pharmacist.

What is the most important information I should know about KAZANO?
KAZANO can cause serious side effects, including:

1. Lactic Acidosis. Metformin, one of the medicines in KAZANO, can cause a rare but serious condition called lactic acidosis (a buildup of an acid in the blood) that can cause death. Lactic acidosis is a medical emergency and must be treated in the hospital.

Call your doctor right away if you have any of the following symptoms, which could be signs of lactic acidosis:

- you feel cold in your hands or feet
- you feel dizzy or lightheaded
- you have a slow or irregular heartbeat
- you feel very weak or tired
- you have unusual (not normal) muscle pain
- you have trouble breathing
- you feel sleepy or drowsy
- you have stomach pains, nausea or vomiting

Most people who have had lactic acidosis with metformin have other things that, combined with metformin, led to the lactic acidosis. Tell your doctor if you have any of the following, because you have a higher chance for getting lactic acidosis with KAZANO if you:

- have severe kidney problems or your kidneys are affected by certain x-ray tests that use injectable dye
- have liver problems
- drink alcohol very often, or drink a lot of alcohol in short-term "binge" drinking
- get dehydrated (lose a large amount of body fluids). This can happen if you are sick with a fever, vomiting, or diarrhea. Dehydration can also happen when you sweat a lot with activity or exercise and do not drink enough fluids
- have surgery
- have a heart attack, severe infection, or stroke

The best way to keep from having a problem with lactic acidosis from metformin is to tell your doctor if you have any of the problems listed above. You doctor may decide to stop KAZANO for a while if you have any of these things.
KAZANO can have other serious side effects. See "What are the possible side effects of KAZANO?"

2. Inflammation of the pancreas (pancreatitis). Alogliptin, one of the medicines in KAZANO, may cause pancreatitis, which may be severe. Certain medical conditions make you more likely to get pancreatitis.

Before you start taking KAZANO:
Tell your doctor if you have ever had:

- pancreatitis
- high blood triglyceride levels

- kidney problems
- stones in your gallbladder (gall stones)

- liver problems
- history of alcoholism

Stop taking KAZANO and call your doctor right away if you have pain in your stomach area (abdomen) that is severe and will not go away. The pain may be felt going from your abdomen through to your back. The pain may happen with or without vomiting. These may be symptoms of pancreatitis.

3. Heart failure: Heart failure means your heart does not pump blood well enough.

Before you start taking KAZANO:
Tell your healthcare provider if you have ever had heart failure or have problems with your kidneys.
Contact your healthcare provider right away if you have any of the following symptoms:

- increasing shortness of breath or trouble breathing especially when lying down

- an unusually fast increase in weight
- unusual tiredness

- swelling of feet, ankles, or legs

These may be symptoms of heart failure.

What is KAZANO?

- KAZANO contains 2 prescription diabetes mellitus medicines, alogliptin (NESINA®) and metformin hydrochloride.
- KAZANO is a prescription medicine used along with diet and exercise to improve blood sugar (glucose) control in adults with type 2 diabetes mellitus.
- KAZANO is not for people with type 1 diabetes mellitus.

It is not known if KAZANO is safe and effective in children under the age of 18.

Who should not take KAZANO?
Do not take KAZANO if you:

- have severe kidney problems
- have a condition called metabolic acidosis or have had diabetic ketoacidosis (increased ketones in your blood or urine)
- are going to get an injection of dye or contrast agents for an x-ray procedure, KAZANO may need to be stopped for a short time. Talk to your doctor about when you should stop KAZANO and when you should start KAZANO again
- are allergic to alogliptin (NESINA) or metformin or any of the ingredients in KAZANO or have had a serious allergic (hypersensitivity) reaction to alogliptin or metformin. See the end of this Medication Guide for a complete list of the ingredients in KAZANO

Symptoms of a serious allergic reaction to KAZANO may include:

- swelling of your face, lips, throat and other areas on your skin
- raised, red areas on your skin (hives)

- difficulty with swallowing or breathing
- skin rash, itching, flaking or peeling

If you have any of these symptoms, stop taking KAZANO and contact your doctor or go to the nearest hospital emergency room right away.

What should I tell my doctor before and during treatment with KAZANO?
Before you take KAZANO, tell your doctor if you:

- have or have had inflammation of your pancreas (pancreatitis)
- have severe kidney or liver problems
- have heart problems, including congestive heart failure
- are going to get an injection of dye or contrast agents for an x-ray procedure, KAZANO may need to be stopped for a short time. Talk to your doctor about when you should stop KAZANO and when you should start KAZANO again
- drink alcohol very often or drink a lot of alcohol in short-term "binge" drinking
- have other medical conditions
- are pregnant or plan to become pregnant. It is not known if KAZANO will harm your unborn baby. Talk with your doctor about the best way to control your blood sugar while you are pregnant or if you plan to become pregnant
- are breastfeeding or plan to breastfeed. It is not known if KAZANO passes into your breast milk. Talk with your doctor about the best way to feed your baby if you are taking KAZANO

Tell your doctor about all the medicines you take, including prescription and over-the-counter medicines, vitamins and herbal supplements. Know the medicines you take. Keep a list of them and show it to your doctor and pharmacist before you start any new medicine.
KAZANO may affect the way other medicines work, and other medicines may affect how KAZANO works. Contact your doctor before you start or stop other types of medicines.

How should I take KAZANO?

- Take KAZANO exactly as your doctor tells you to take it.
- Take KAZANO 2 times each day.
- Take KAZANO with food to lower your chances of having an upset stomach.
- Do not break or cut KAZANO tablets before swallowing.
- Your doctor may need to change your dose of KAZANO to control your blood glucose. Do not change your dose unless told to do so by your doctor.
- If you miss a dose, take it as soon as you remember. If you do not remember until it is time for your next dose, skip the missed dose, and take the next dose at your regular time. Do not take 2 doses of KAZANO at the same time.
- If you take too much KAZANO, call your doctor or your Poison Help Line right away at 1-800-222-1222.
- If your body is under stress, such as from fever, infection, accident or surgery, the dose of your diabetes mellitus medicines may need to be changed. Call your doctor right away.
- Stay on your diet and exercise programs and check your blood sugar as your doctor tells you to.
- Your doctor may do certain blood tests before you start KAZANO and during treatment as needed. Your doctor may ask you to stop taking KAZANO based on the results of your blood tests due to how well your kidneys are working.
- Your doctor will check your diabetes mellitus with regular blood tests, including your blood sugar levels and your hemoglobin A1C.

What are the possible side effects of KAZANO?
KAZANO can cause serious side effects, including:

- See "What is the most important information I should know about KAZANO?"
- Serious allergic (hypersensitivity) reactions, such as:

- swelling of your face, lips, throat and other areas on your skin
- raised, red areas on your skin (hives)

- difficulty swallowing or breathing
- skin rash, itching, flaking or peeling

If you have these symptoms, stop taking KAZANO and contact your doctor right away or go to the nearest hospital emergency room.

- Liver problems. Call your doctor right away or go to the nearest hospital emergency room if you have unexplained symptoms, such as:

- nausea or vomiting
- loss of appetite

- stomach pain
- dark urine

- unusual or unexplained tiredness
- yellowing of your skin or the whites of your eyes

- Low Vitamin B12 levels. Some people taking metformin one of the medicines in KAZANO had low levels of Vitamin B12. Your doctor should do blood tests every year and check your Vitamin B12 levels every 2 to 3 years while you are taking KAZANO.
- Low blood sugar (hypoglycemia). If you take KAZANO with another medicine that can cause low blood sugar, such as a sulfonylurea or insulin, your risk of getting low blood sugar is higher. The dose of your sulfonylurea medicine or insulin may need to be lowered while you take KAZANO. If you have symptoms of low blood sugar, you should check your blood sugar and treat if low, and then call your doctor. Signs and symptoms of low blood sugar may include:

- shaking or feeling jittery
- sweating

- fast heartbeat
- change in vision

- hunger
- headache

- change in mood
- confusion

- dizziness

- Joint pain. Some people who take medicines called DPP-4 inhibitors, one of the medicines in KAZANO, may develop joint pain that can be severe. Call your doctor if you have severe joint pain.
- Skin reaction. Some people who take medicines called DPP-4 inhibitors, one of the medicines in KAZANO, may develop a skin reaction called bullous pemphigoid that can require treatment in a hospital. Tell your doctor right away if you develop blisters or the breakdown of the outer layer of your skin (erosion). Your doctor may tell you to stop taking KAZANO.

The most common side effects of KAZANO include:

- cold-like symptoms (upper respiratory tract infection)
- increase in blood pressure
- urinary tract infection

- stuffy or runny nose and sore throat
- headache

- diarrhea
- back pain

Taking KAZANO with food can help lessen the common stomach side effects of metformin that usually happen at the beginning of treatment. If you have unexplained stomach problems, tell your doctor. Stomach problems that start later, during treatment, may be a sign of something more serious.
Tell your doctor if you have any side effect that bothers you or that does not go away.
These are not all the possible side effects of KAZANO. For more information, ask your doctor or pharmacist.
Call your doctor for medical advice about side effects. You may report side effects to FDA at 1-800-FDA-1088.

How should I store KAZANO?

- Store KAZANO at room temperature between 68°F to 77°F (20°C to 25°C).
- Keep the container of KAZANO tightly closed.

Keep KAZANO and all medicines out of the reach of children.

General information about the safe and effective use of KAZANO
Medicines are sometimes prescribed for purposes other than those listed in the Medication Guide. Do not take KAZANO for a condition for which it was not prescribed. Do not give KAZANO to other people, even if they have the same symptoms you have. It may harm them.
This Medication Guide summarizes the most important information about KAZANO. If you would like to know more information, talk with your doctor. You can ask your doctor or pharmacist for information about KAZANO that is written for health professionals.
For more information go to www.kazano.com or call 1-877-TAKEDA-7 (1-877-825-3327).

What are the ingredients in KAZANO?
Active ingredients: alogliptin and metformin hydrochloride
Inactive ingredients: crospovidone, magnesium stearate, mannitol, microcrystalline cellulose, and povidone; the tablets are film-coated with ferric oxide yellow, hypromellose 2910, talc, and titanium dioxide.
Distributed by Takeda Pharmaceuticals America, Inc., Cambridge, MA 02142.
KAZANO and NESINA are registered trademarks of Takeda Pharmaceutical Company Limited.
©2025 Takeda Pharmaceuticals America, Inc. All rights reserved.

This Medication Guide has been approved by the U.S. Food and Drug Administration.

ALM143 R15 February 2025

PRINCIPAL DISPLAY PANEL - 12.5 mg/500 mg Bottle Label

NDC 64764-335-60

Kazano®

(alogliptin and
metformin HCl) tablets

12.5* mg/500 mg

Dispense with
Medication Guide

60 Tablets

Takeda

Rx Only

PRINCIPAL DISPLAY PANEL - 12.5 mg/1000 mg Bottle Label

NDC 64764-337-60

Kazano®

(alogliptin and
metformin HCl) tablets

12.5* mg/1000 mg

Dispense with
Medication Guide

60 Tablets

Takeda

Rx Only